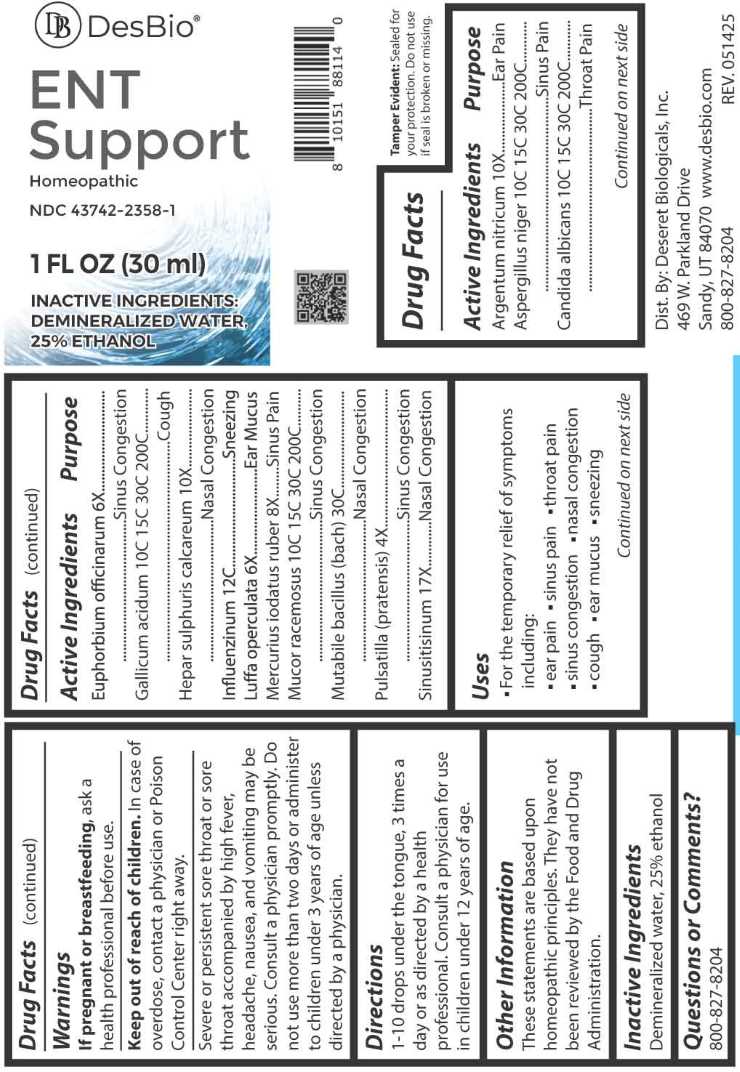 DRUG LABEL: ENT Support
NDC: 43742-2358 | Form: LIQUID
Manufacturer: Deseret Biologicals, Inc.
Category: homeopathic | Type: HUMAN OTC DRUG LABEL
Date: 20260223

ACTIVE INGREDIENTS: SILVER NITRATE 10 [hp_X]/1 mL; ASPERGILLUS NIGER VAR. NIGER 10 [hp_C]/1 mL; CANDIDA ALBICANS 10 [hp_C]/1 mL; EUPHORBIA RESINIFERA RESIN 6 [hp_X]/1 mL; GALLIC ACID MONOHYDRATE 10 [hp_C]/1 mL; CALCIUM SULFIDE 10 [hp_X]/1 mL; INFLUENZA A VIRUS A/VICTORIA/4897/2022 IVR-238 (H1N1) ANTIGEN (FORMALDEHYDE INACTIVATED) 12 [hp_C]/1 mL; INFLUENZA A VIRUS A/THAILAND/8/2022 IVR-237 (H3N2) ANTIGEN (FORMALDEHYDE INACTIVATED) 12 [hp_C]/1 mL; INFLUENZA B VIRUS B/AUSTRIA/1359417/2021 BVR-26 WHOLE 12 [hp_C]/1 mL; INFLUENZA B VIRUS B/PHUKET/3073/2013 BVR-1B WHOLE 12 [hp_C]/1 mL; LUFFA OPERCULATA FRUIT 6 [hp_X]/1 mL; MERCURIC IODIDE 8 [hp_X]/1 mL; MUCOR RACEMOSUS 10 [hp_C]/1 mL; ESCHERICHIA COLI 30 [hp_C]/1 mL; PULSATILLA PRATENSIS WHOLE 4 [hp_X]/1 mL; SINUSITISINUM 17 [hp_X]/1 mL
INACTIVE INGREDIENTS: WATER; ALCOHOL

DRUG FACTS:

ACTIVE INGREDIENTS:

Argentum Nitricum 10X, Aspergillus Niger 10C, 15C, 30C, 200C, Candida Albicans 10C, 15C, 30C, 200C, Euphorbium Officinarum 6X, Gallicum Acidum 10C, 15C, 30C, 200C, Hepar Sulphuris Calcareum 10X, Influenzinum 12C, Luffa Operculata 6X, Mercurius Iodatus Ruber 8X, Mucor Racemosus 10C, 15C, 30C, 200C, Mutabile Bacillus (Bach) 30C, Pulsatilla (Pratensis) 4X, Sinusitisinum 17X.

PURPOSE:

Argentum Nitricum – Ear Pain, Aspergillus Niger – Sinus Pain, Candida Albicans – Throat Pain, Euphorbium Officinarum – Sinus Congestion, Gallicum Acidum - Cough, Hepar Sulphuris Calcareum – Nasal Congestion, Influenzinum - Sneezing, Luffa Operculata – Ear Mucus, Mercurius Iodatus Ruber – Sinus Pain, Mucor Racemosus – Sinus Congestion, Mutabile Bacillus (Bach) – Nasal Congestion, Pulsatilla (Pratensis) – Sinus Congestion, Sinusitisinum – Nasal Congestion

USES:

• For the temporary relief of symptoms including:

• ear pain • sinus pain • throat pain • sinus congestion

• nasal congestion • cough • ear mucus • sneezing

These statements are based upon homeopathic principles. They have not been reviewed by the Food and Drug Administration.

WARNINGS:

If pregnant or breastfeeding, ask a health professional before use.

Keep out of reach of children. In case of overdose, contact a physician or Poison Control Center right away.

Severe or persistent sore throat or sore throat accompanied by high fever, headache, nausea, and vomiting may be serious. consult a physician promptly. Do not use more than two days or administer to children under 3 years of age unless directed by a physician.

Tamper Evident: Sealed for your protection. Do not use if seal is broken or missing.

KEEP OUT OF REACH OF CHILDREN:

In case of overdose, contact a physician or Poison Control Center right away.

DIRECTIONS:

1-10 drops under the tongue, 3 times a day or as directed by a health professional. Consult a physician for use in children under 12 years of age.

INACTIVE INGREDIENTS:

Demineralized water, 25% ethanol

QUESTIONS:

Dist. By: Deseret Biologicals, Inc.

469 W. Parkland Drive

Sandy, UT 84070

www.desbio.com

800-827-8204

PACKAGE LABEL DISPLAY:

DesBio

ENT Support

Homeopathic

NDC 43742-2358-1

1 FL OZ (30 ml)